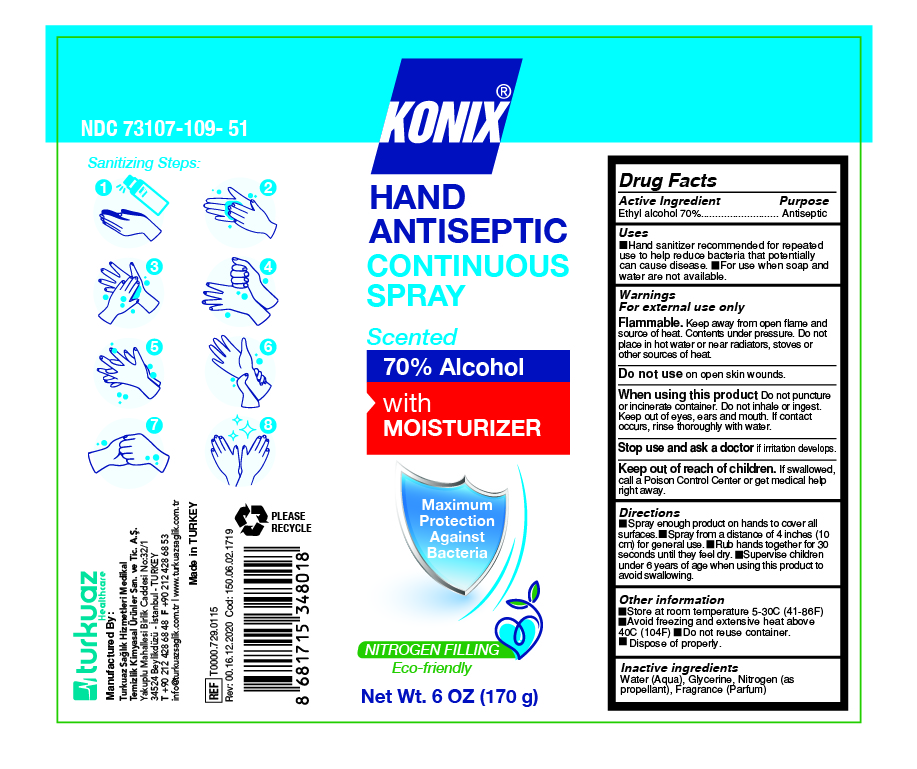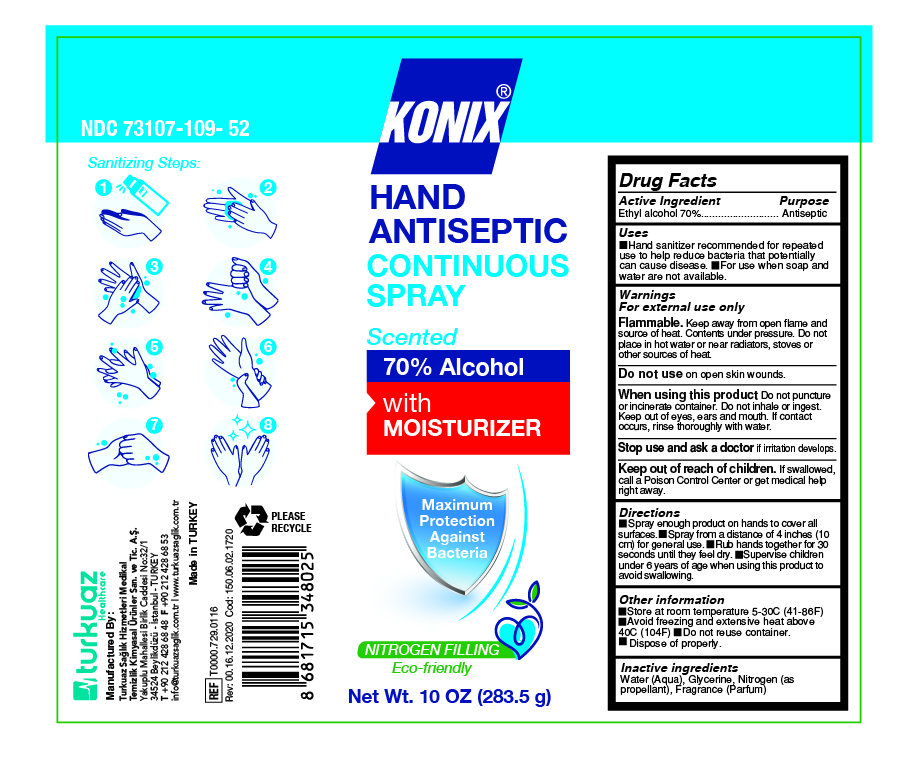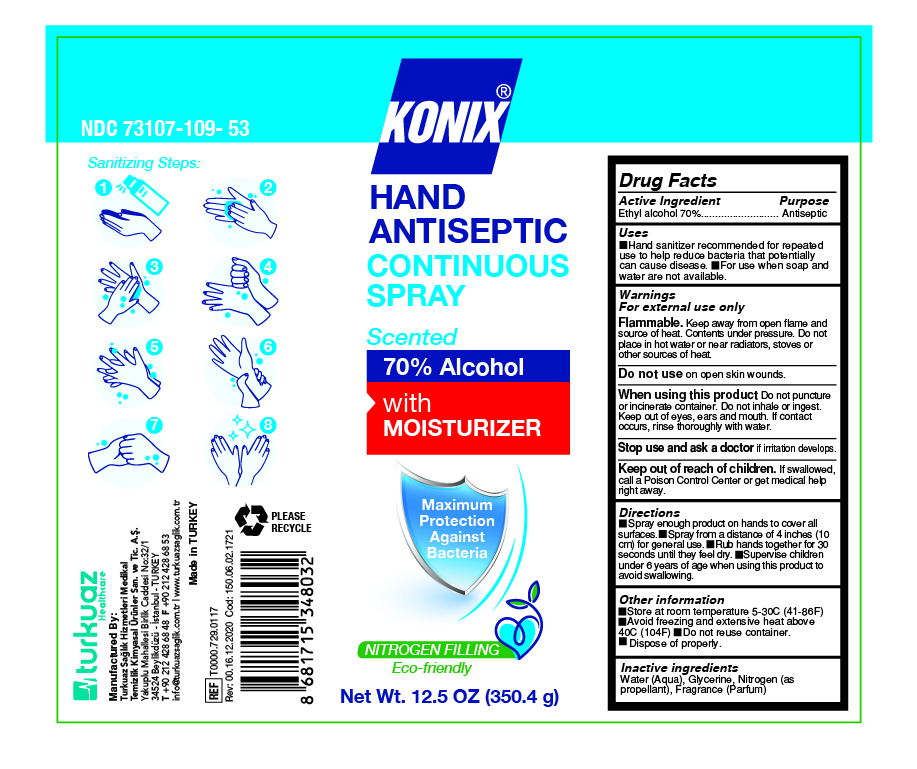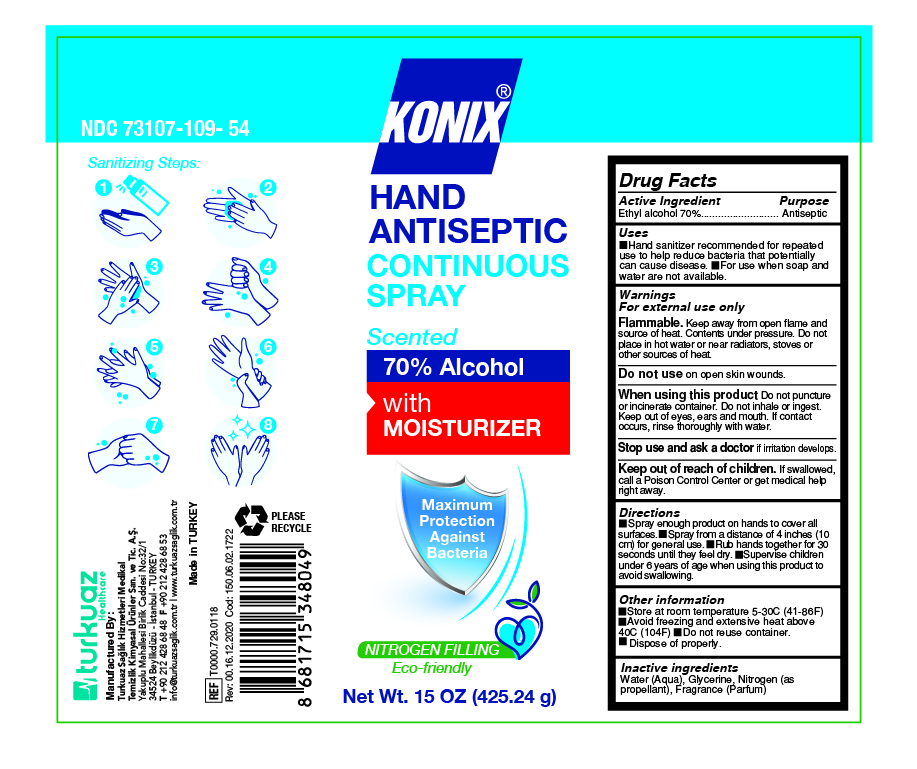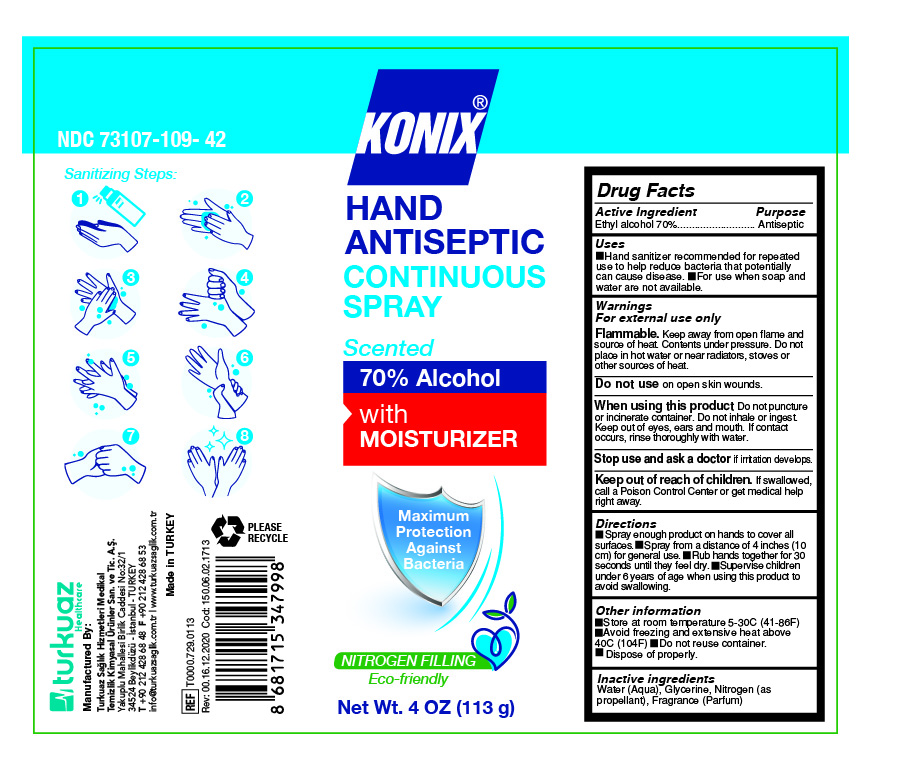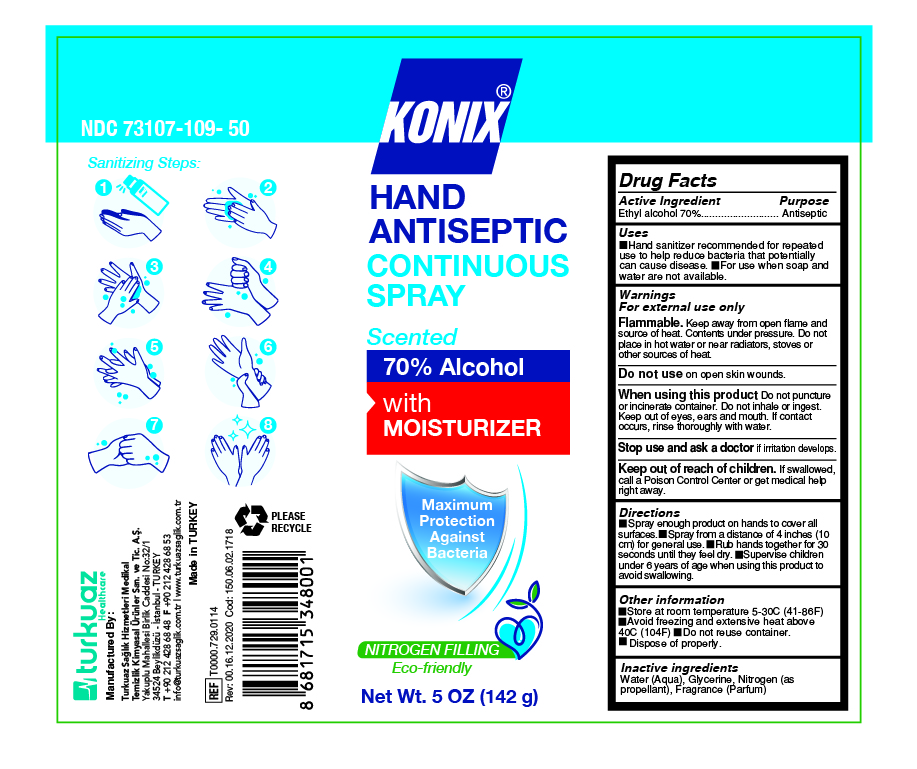 DRUG LABEL: Konix Hand Antiseptic
NDC: 73107-109 | Form: AEROSOL, SPRAY
Manufacturer: Turkuaz Saglik Hizmetleri Medikal Temizlik Kimyasal Urunler
Category: otc | Type: HUMAN OTC DRUG LABEL
Date: 20210127

ACTIVE INGREDIENTS: ALCOHOL 70 g/100 g
INACTIVE INGREDIENTS: WATER; GLYCERIN; NITROGEN

Konix Hand Antiseptic Spray

Active Ingredient(s)

Ethyl Alcohol 70%

Purpose

Antiseptic

Use

Hand sanitizer recommended for repeated useto help reduce bacteria that potentially can cause disease. For use when soap and water are not available.

For External use only

Flammable. Keep away from open flame and source of heat. Contents under pressure. Do not place in hot water or near radiators, stoves or other sources of heat.

Do not use

on open skin wounds

When using this product

Do not puncture or incinerate container. Do not inhale or ingest. Keep out of eyes, ears and mouth. If contact occurs, rinse thoroughly with water.

Stop use and ask a doctor

if irritation develops

Keep out of reach of children.

If swallowed, call a Poison Control Center right away

Directions

Spray enough product on hands to cover all surfaces. Spray from a distance of 4 inches (10cm) for general use. Rub hands together for 30 seconds until they feel dry.
Supervise children under 6 years of age when using this product to avoid swallowing.

Other Information

Store at room temperature 5-30C (41-86F). Avoid freezing and excessive heat above 40 C (104F). Do not reuse container. Dispose of properly.

Inactive ingredients

Water (aqua), Glycerine, Nitrogen (as propellant), Fragrance(Parfum)

Konix Hand Antiseptic

Continuous Spray

Scented

70% Alcohol

wiht Moisturizer

Net 4OZ (113g)

Konix Hand Antiseptic

Continuous Spray

Scented

70% Alcohol

with Moisturizer

Net 5 OZ (142g)

Konix Hand Antiseptic

Continuous Spray

Scented

70% Alcohol

with Moisturizer

Net 6 OZ (170g)

Konix Hand Antiseptic

Continuous Spray

Scented

70% Alcohol

with Moisturizer

Net 10 Oz (283.5g)

Konix Hand Antiseptic

Continuous Spray

Scented

70% Alcohol

with Moisturizer

Net 12.5OZ (350.4g)

Konix Hand Antiseptic

Continuous Spray

Scented

70% Alcohol

with Moisturizer

Net 15 OZ (425.24g)